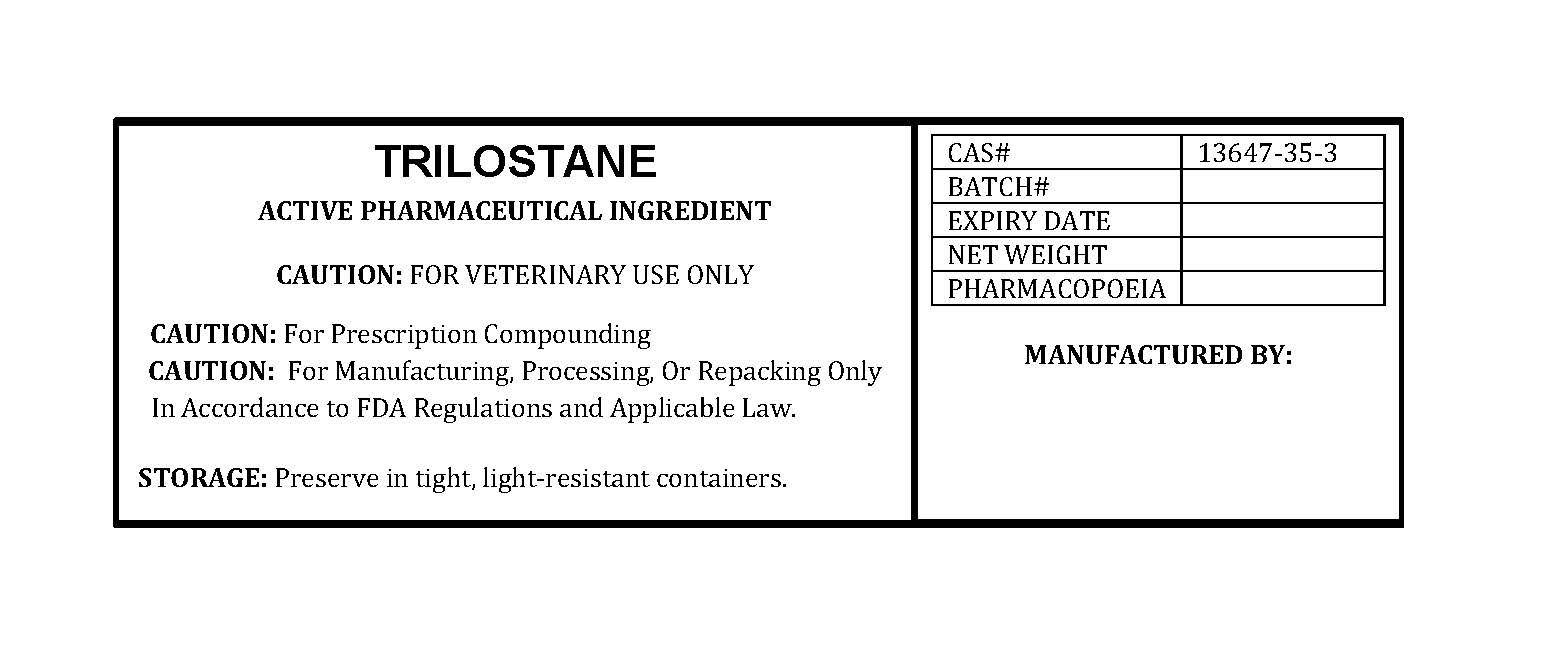 DRUG LABEL: TRILOSTANE
NDC: 86184-394 | Form: POWDER
Manufacturer: MAEDA INC
Category: other | Type: BULK INGREDIENT - ANIMAL DRUG
Date: 20250820

ACTIVE INGREDIENTS: TRILOSTANE 1 g/1 g

TRILOSTANE

PACKAGE LABEL

trilostanelabelfile.jpg